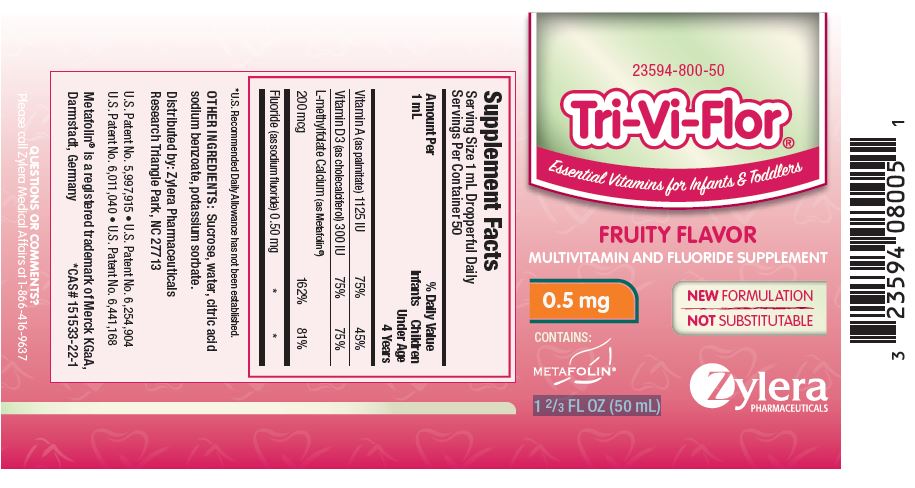 DRUG LABEL: Tri-Vi-Flor
NDC: 23594-800 | Form: SUSPENSION/ DROPS
Manufacturer: Aytu Therapeutics, LLC
Category: other | Type: DIETARY SUPPLEMENT
Date: 20190408

ACTIVE INGREDIENTS: VITAMIN A 1125 [iU]/50 mL; CHOLECALCIFEROL 300 [iU]/50 mL; LEVOMEFOLATE CALCIUM 200 ug/50 mL; FLUORIDE ION 0.5 mg/50 mL
INACTIVE INGREDIENTS: SUCROSE; WATER; CITRIC ACID MONOHYDRATE; SODIUM BENZOATE; POTASSIUM SORBATE

HEALTH CLAIM

Multivitamin and Fluoride Supplement

Supplement Facts
Serving Size 1 mL Dropperful Daily Servings Per Container 50
 | % Daily Value
Amount Per 1 mL | Infants | Children Under Age 4 Years
Vitamin A (as palmitate) 1125 IU | 75% | 45%
Vitamin D3 (as cholecalciferol) 300 IU | 75% | 75%
L-methylfolate Calcium (as Metafolin®) 200 mcg | 162% | 81%
Fluoride (as sodium fluoride) 0.50 mg | * | *

*U.S. Recommended Daily Allowance has not been established

OTHER INGREDIENTS: Sucrose, water, citric acid, sodium benzoate, potassium sorbate.

Distributed by: Zylera Pharmaceuticals
Research Triangle Park, NC 27713

U.S. Patent No. 5,997,915 • U.S. Patent No. 6,254,904
U.S. Patent No. 6,011,040 • U.S. Patent No. 6,441,168

Metafolin® is a registered trademark of Merck KGaA, Darmstadt, Germany *CAS# 151533-22-1

QUESTIONS OR COMMENTS? Please call Zylera Medical Affairs at 1-866-416-9637

How to Use the Enclosed Dropper

Fill the dropper to the 1 mL line to provide the full daily dosage. Use full dosage, regardless of age or weight, unless your child's doctor recommends a different dosage. Dispense with a single squeeze of the dropper bulb. It is normal for a small amount to remain in the tip.

Dosing Tips

Drops may be given by dispensing directly into the mouth. Drops may also be mixed with formula, fruit juice, cereal or other foods to increase your child's acceptance.

SAFE HANDLING WARNING

Shake well before use.

This product comes with a child-resistant cap. Refrigeration not required. After opening, store away from direct sunlight.

WARNING

As with medicines, keep out of the reach of children.

PRINCIPAL DISPLAY PANEL - Tri-Vi-Flor with 0.5 mg of Fluoride

23594-800-50

Tri-Vi-Flor

Essential Vitamins for Infants & Toddlers

FRUITY FLAVOR

MULTIVITAMIN AND FLUORIDE SUPPLEMENT

0.5 mg

NEW FORMULATION
NOT SUBSTITUTABLE

CONTAINS: METAFOLIN

1 2/3 FL OZ (50 mL)

Zylera Pharmaceuticals